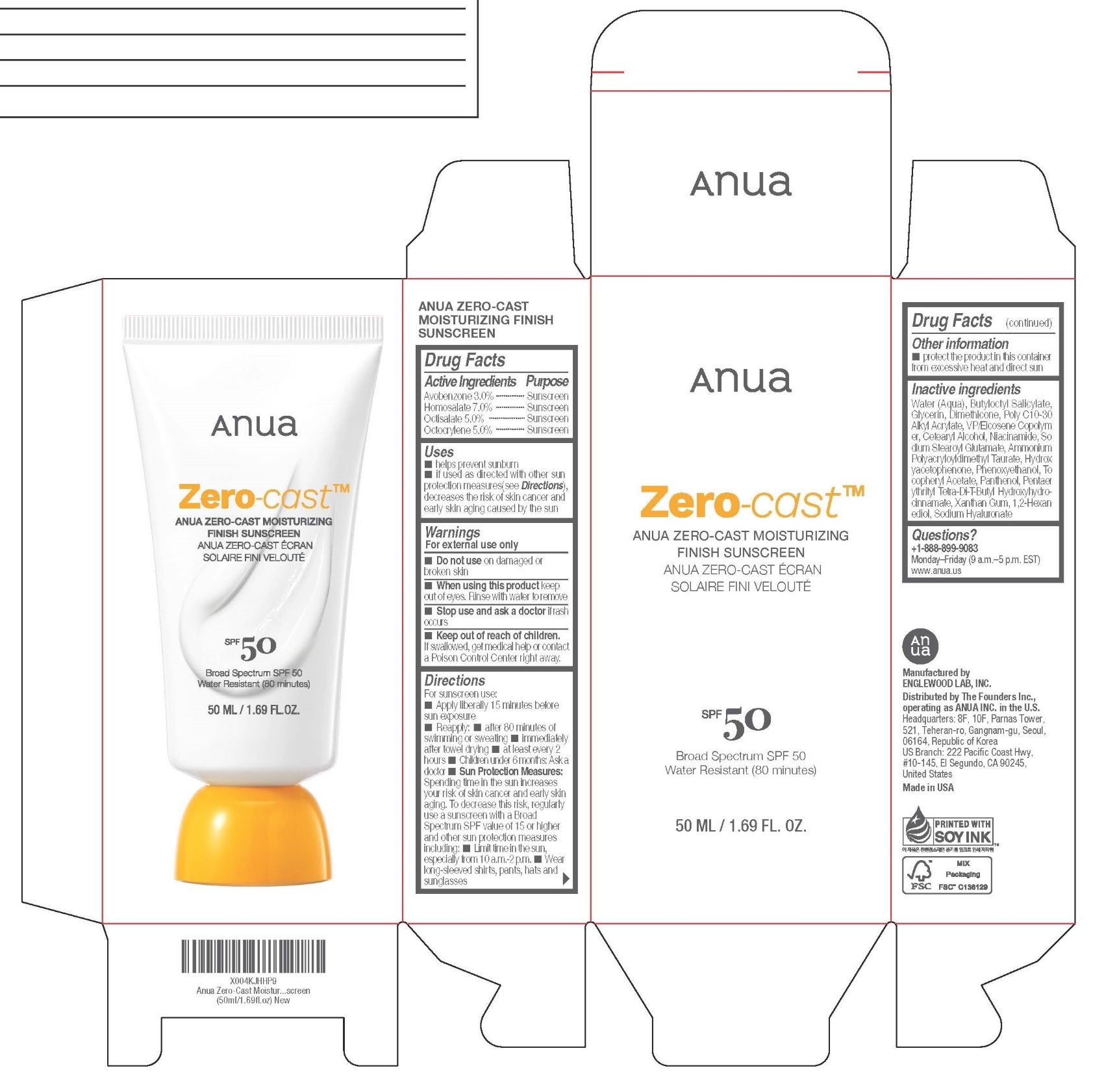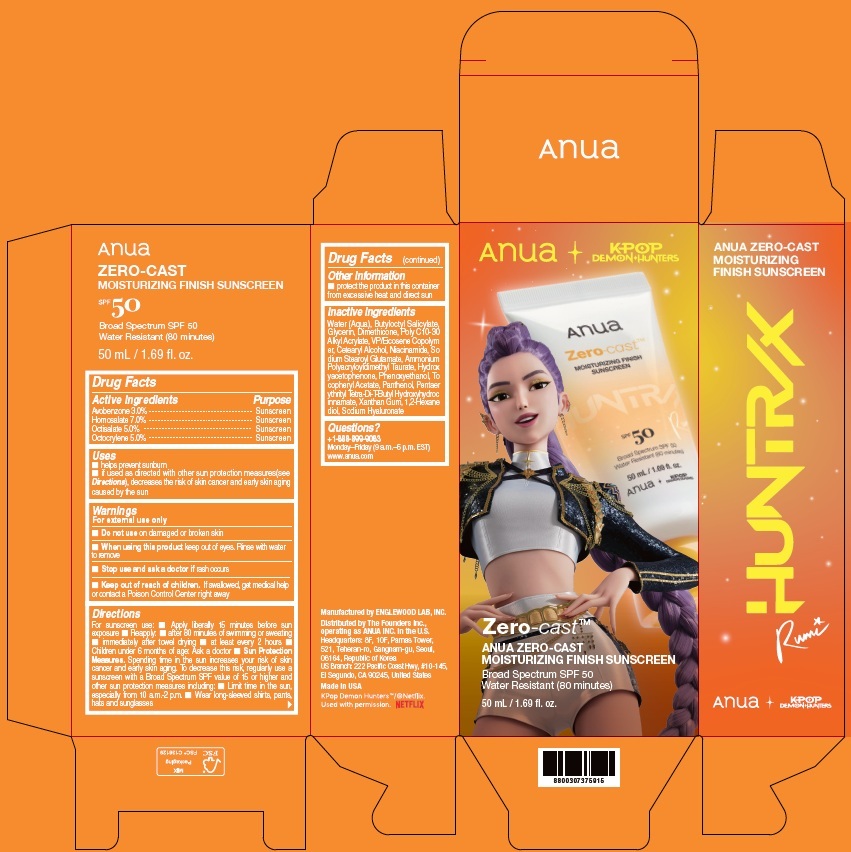 DRUG LABEL: ANUA ZERO-CAST MOISTURIZING FINISH SUNSCREEN
NDC: 84610-200 | Form: CREAM
Manufacturer: The Founders Inc.
Category: otc | Type: HUMAN OTC DRUG LABEL
Date: 20260119

ACTIVE INGREDIENTS: AVOBENZONE 30 mg/1 mL; HOMOSALATE 70 mg/1 mL; OCTISALATE 50 mg/1 mL; OCTOCRYLENE 50 mg/1 mL
INACTIVE INGREDIENTS: SODIUM STEAROYL GLUTAMATE; AMMONIUM POLYACRYLOYLDIMETHYL TAURATE; CETEARYL ALCOHOL; NIACINAMIDE; 1,2-HEXANEDIOL; PENTAERYTHRITYL TETRA-DI-T-BUTYL HYDROXYHYDROCINNAMATE; SODIUM HYALURONATE; WATER; XANTHAN GUM; ALPHA-TOCOPHEROL ACETATE; GLYCERIN; HYDROXYACETOPHENONE; BUTYLOCTYL SALICYLATE; DIMETHICONE; PANTHENOL; VINYLPYRROLIDONE/EICOSENE COPOLYMER; PHENOXYETHANOL

ANUA ZERO-CAST MOISTURIZING FINISH SUNSCREEN BROAD SPECTRUM SPF 50 Water Resistant (80 minutes)

Drug Facts

Active Ingredients

Avobenzone 3.0%

Homosalate 7.0%

Octisalate 5.0%

Octocrylene 5.0%

Purpose

Sunscreen

Uses

■ helps prevent sunburn
■ if used as directed with other sun protection measures(see Directions), decreases the risk of skin cancer and early skin aging caused by the sun

Warnings

For external use only

Do not use

■ on damaged or broken skin

When using this product

■ keep out of eyes. Rinse with water to remove

Stop use and ask a doctor if

■ rash occurs

Keep out of reach of children.

If swallowed, get medical help or contact a Poison Control Center right away.

Directions

For sunscreen use:

■ Apply liberally 15 minutes before sun exposure

■ Reapply:

■ after 80 minutes of swimming or sweating

■ immediately after towel drying

■ at least every 2 hours

■ Children under 6 months of age: Ask a doctor

■ Sun Protection Measures. Spending time in the sun increases your risk of skin cancer and early skin aging. To decrease this risk, regularly use a sunscreen with a Broad Spectrum SPF value of 15 or higher and other sun protection measures including:

■ limit time in the sun, especially from 10 a.m.- 2 p.m.

■ wear long-sleeved shirts, pants, hats, and sunglasses

Other information

■ Protect the product in this container from excessive heat and direct sun

Inactive ingredients

Water (Aqua), Butyloctyl Salicylate, Glycerin, Dimethicone, Poly C10-30 Alkyl Acrylate, VP/Eicosene Copolymer, Cetearyl Alcohol, Niacinamide, Sodium Stearoyl Glutamate, Ammonium Polyacryloyldimethyl Taurate, Hydroxyacetophenone, Phenoxyethanol, Tocopheryl Acetate, Panthenol, Pentaerythrityl Tetra-Di-T-Butyl Hydroxyhydrocinnamate, Xanthan Gum, 1,2-Hexanediol, Sodium Hyaluronate

Questions?

+1-888-899-9083

Monday–Friday (9 a.m.–5 p.m. EST)

www.anua.us